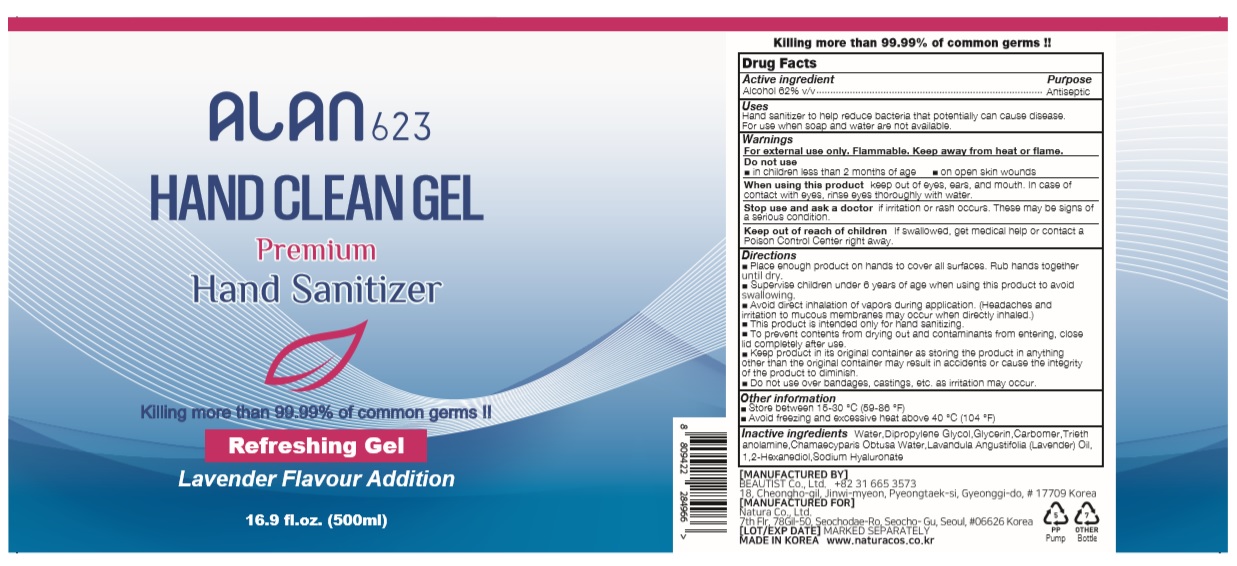 DRUG LABEL: ALAN623 HAND CLEAN Gel
NDC: 70987-562 | Form: GEL
Manufacturer: BEAUTIST CO., LTD.
Category: otc | Type: HUMAN OTC DRUG LABEL
Date: 20200420

ACTIVE INGREDIENTS: ALCOHOL 310 mL/500 mL
INACTIVE INGREDIENTS: LAVENDER OIL; DIPROPYLENE GLYCOL; GLYCERIN; TROLAMINE; CHAMAECYPARIS OBTUSA WOOD OIL; WATER; 1,2-HEXANEDIOL; CARBOMER HOMOPOLYMER, UNSPECIFIED TYPE; HYALURONATE SODIUM

500ml_62%_gel_ALAN623 HAND CLEAN Gel [70987-562-01]